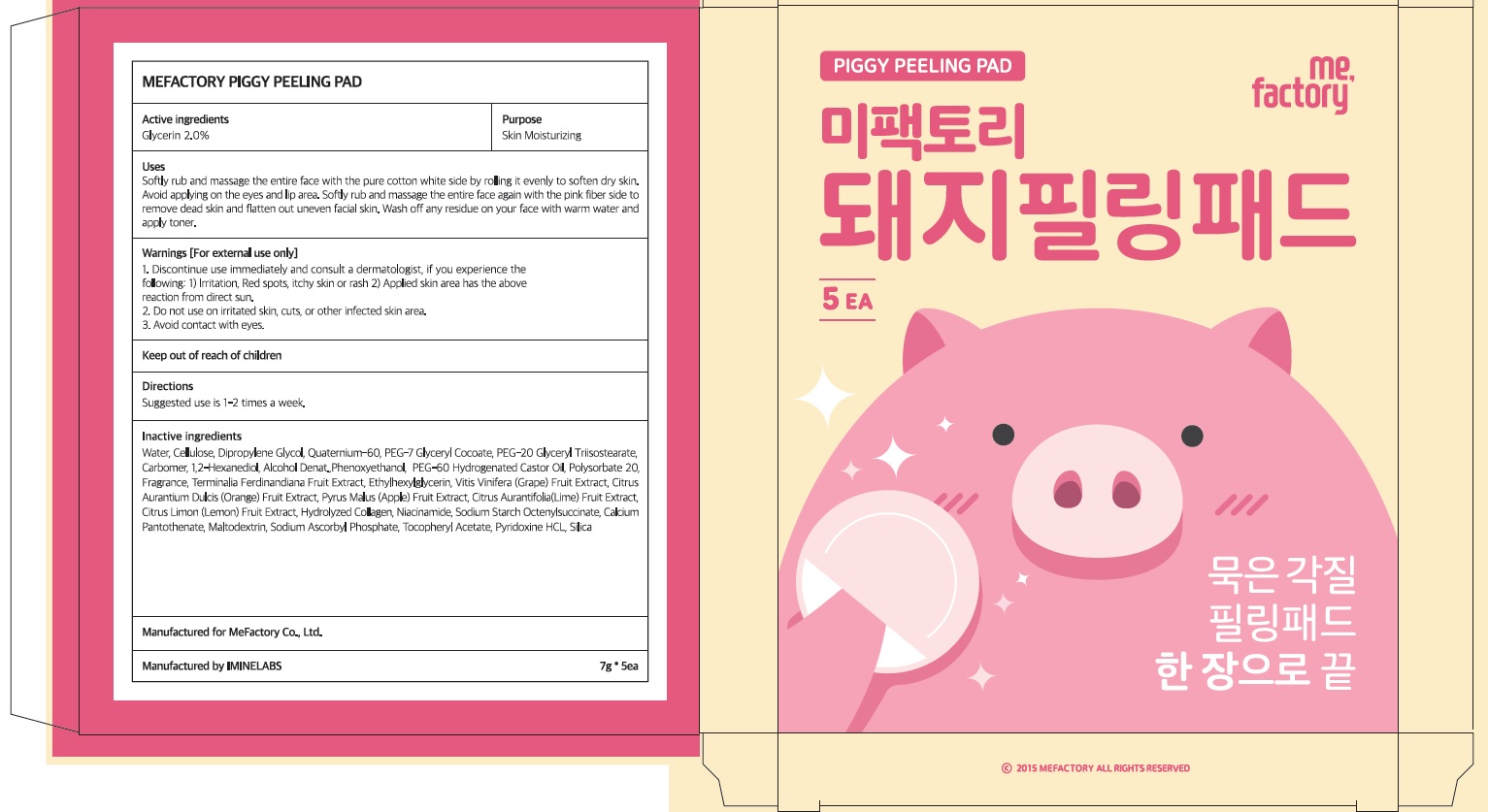 DRUG LABEL: Mefactory Piggy Peeling Pad
NDC: 70908-150 | Form: PATCH
Manufacturer: MeFactory Co., Ltd.
Category: otc | Type: HUMAN OTC DRUG LABEL
Date: 20181129

ACTIVE INGREDIENTS: Glycerin 0.14 g/7 g
INACTIVE INGREDIENTS: WATER; Dipropylene Glycol

ACTIVE INGREDIENT

Active ingredients: Glycerin 2.0%

INACTIVE INGREDIENT

Inactive ingredients: Water, Cellulose, Dipropylene Glycol, Quaternium-60, PEG-7 Glyceryl Cocoate, PEG-20 Glyceryl Triisostearate, Carbomer, 1,2-Hexanediol, Alcohol Denat.,Phenoxyethanol, PEG-60 Hydrogenated Castor Oil, Polysorbate 20, Fragrance, Terminalia Ferdinandiana Fruit Extract, Ethylhexylglycerin, Vitis Vinifera (Grape) Fruit Extract, Citrus Aurantium Dulcis (Orange) Fruit Extract, Pyrus Malus (Apple) Fruit Extract, Citrus Aurantifolia (Lime) Fruit Extract, Citrus Limon (Lemon) Fruit Extract, Hydrolyzed Collagen, Niacinamide, Sodium Starch Octenylsuccinate, Calcium Pantothenate, Maltodextrin, Sodium Ascorbyl Phosphate, Tocopheryl Acetate, Pyridoxine HCL, Silica,

PURPOSE

Purpose: Skin Moisturizing

WARNINGS

Warnings: For external use only. 1. Discontinue use immediately and consult a dermatologist, if you experience the following: 1) Irritation, Red spots, itchy skin or rash 2) Applied skin area has the above reaction from direct sun 2. Do not use on irritated skin, cuts, or other infected skin area. 3. Avoid contact with eyes.

KEEP OUT OF REACH OF CHILDREN

Uses

Uses: Softly rub and massage the entire face with the pure cotton white side by rolling it evenly to soften dry skin. Avoid applying on the eyes and lip area. Softly rub and massage the entire face again with the pink fiber side to remove dead skin and flatten out uneven facial skin. Wash off any residue on your face with warm water and apply toner.

Directions

Directions: Suggested use is 1-2 times a week